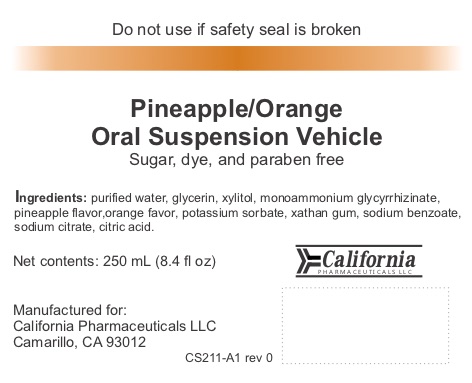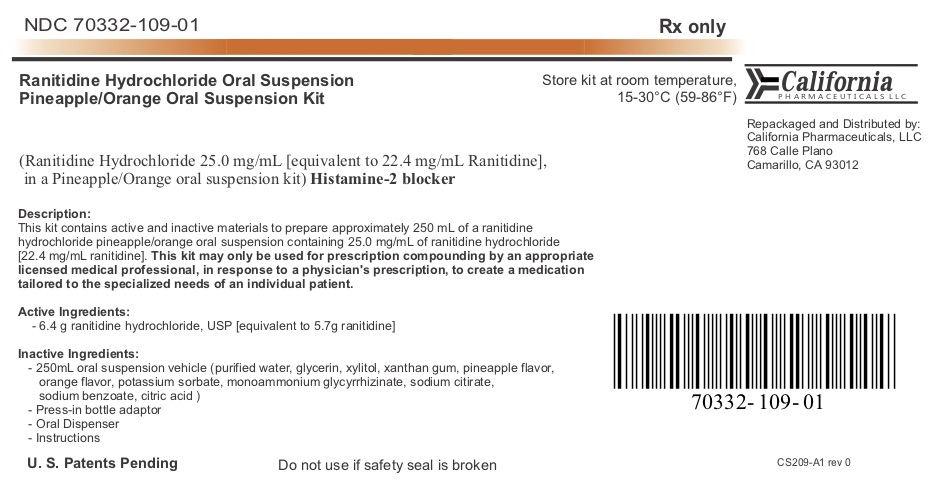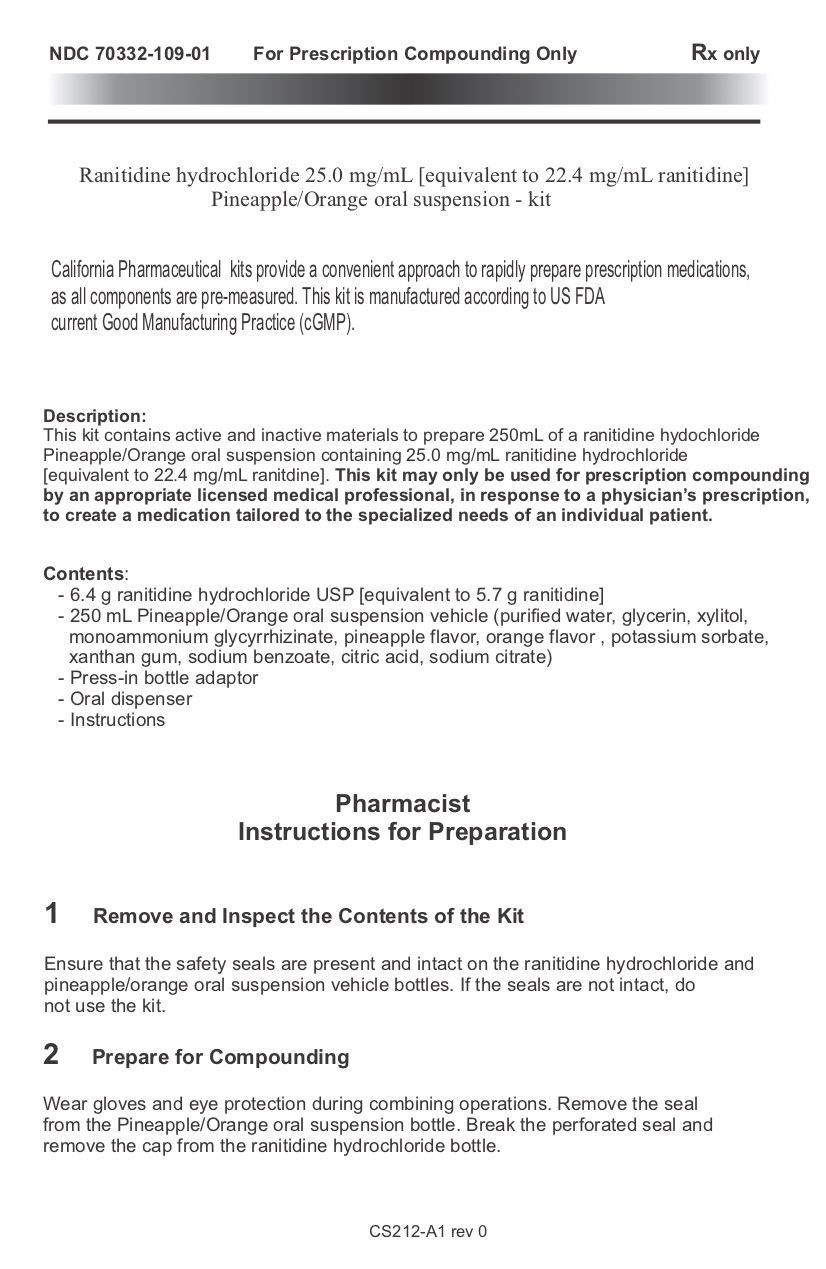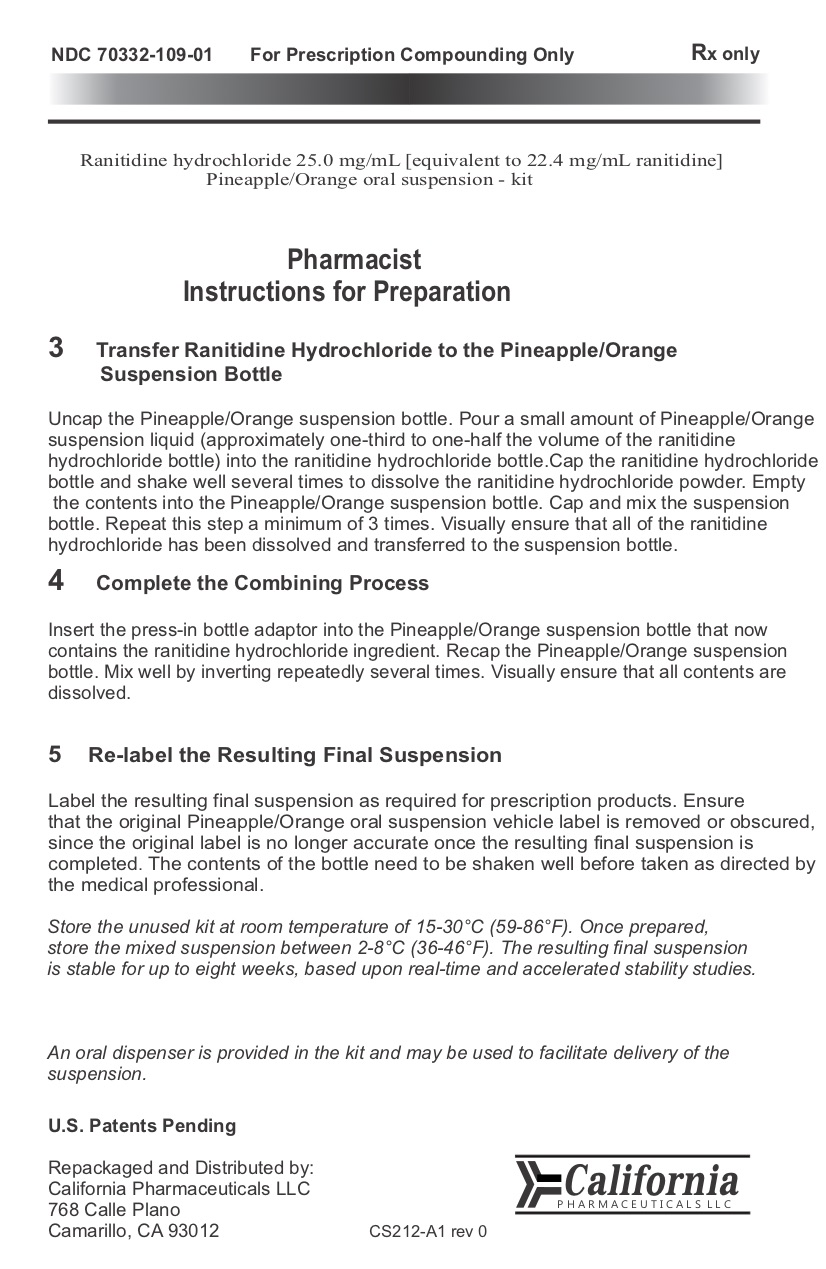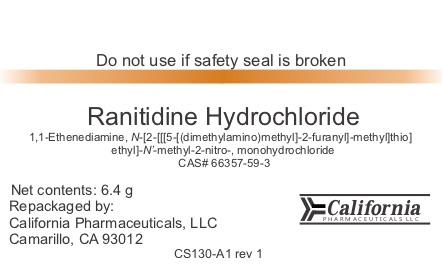 DRUG LABEL: Ranitidine Hydrochloride Oral Suspension Kit
NDC: 70332-109 | Form: KIT | Route: ORAL
Manufacturer: California Pharmaceuticals, LLC
Category: prescription | Type: HUMAN PRESCRIPTION DRUG LABEL
Date: 20180105

ACTIVE INGREDIENTS: RANITIDINE HYDROCHLORIDE 6.4 g/6.4 g
INACTIVE INGREDIENTS: WATER; GLYCERIN; XYLITOL; AMMONIUM GLYCYRRHIZATE; POTASSIUM SORBATE; XANTHAN GUM; SODIUM BENZOATE; SODIUM CITRATE; CITRIC ACID MONOHYDRATE

Ranitidine Hydrochloride Oral Suspension
Pineapple/Orange Oral Suspension Kit
Repackaged 70332-109

Instructions for Preparation Page 1 Page 2

NDC 70332-109-01

For Prescription Compunding Only

Rx only

Ranitidine Hydrochloride Oral Suspension

Ranitidine hydrochloride 25.0mg/mL [equivalent to 22.4 mg/mL rantidine]

Pineapple/Orange oral suspension - kit

Ranitidine Hydrochloride Oral Suspension kits provide a convenient approach to rapidly prepare prescription medications, as all components are pre-measured. This kit is manufactured according to US FDA current Good Manufacturing Practice (cGMP).

Description:

This kit contains active and inactive materials to prepare 250mL of a ranitidine hydochloride Pineapple/Orange oral suspension containing 25.0 mg/mL ranitidine Hydrochloride [equivalent to 22.4 mg/mL ranitidine]. This kit may only be used for prescriptioncompounding by an appropriate licensed medical professional, in response to a physician's prescription, to create a medication tailored to the specialized needs of an individual patient.

Contents:

- 6.4 ranitidine hydrochloride USP [equivalent to 5.7 g ranitidine]

- 250mL Pineapple/Orange oral suspension vehicle (purified water, glycerin, xylitol, monoammoniumium glycyrrhizinate, pineapple flavor,

orange flavor, potassium sorbate, xanthan gum, sodium benzoate, citric acid, sodium

citrate)

- Press-in bottle adaptor

- Oral dispenser

- Instructions

Pharmacist Instructions for Preparation

1 Remove and Inspect the Contents of the Kit

Ensure that the safety seals are present and intact on the ranitidine hydrochloride and pineapple/orange oral suspension vehicle bottles. If the seals are not intact, do not use the kit.

2 Prepare for Compounding

Wear gloves and eye protection during combining operations. Remove the seal from the Pineapple/Orange oral suspension bottle. Break the perforated seal and remove the cap from the ranitidine hydrochloride bottle.

3 Transfer Ranitidine Hydrochloride to the Pineapple/Orange Suspension Bottle

Uncap the Pineapple/Orange suspension bottle. Pour a small amount of Pineapple/Orange suspension liquid (approximately one-third to one-half the volume of the ranitidine hydrochloride bottle) into the ranitidine hydrochloride bottle. Cap the ranitidine hydrochloride bottle and shake well several times to dissolve the ranitidine hydrochloride powder. Empty the contents into the Pineapple/Orange suspension bottle. Cap and mix the suspension bottle. Repeat this step a minimum of 3 times. Visually ensure that all of the renitidine hydrochloride has been dissolved and transferred to the suspension bottle.

4 Completing the Compounding Process

Insert the press-in bottle adaptor into the Pineapple/Orange suspension bottle that now contains the renitidine hydrochloride. Recap the Pineapple/Orange suspension bottle. Mix well by inverting repestedly several times. Visually ensure that all contents are dissolved.

5 Re-label the Resulting Final Suspension

Label the resulting final suspension as required for prescription products. Ensure that the original Pineapple/Orange oral suspension vehicle label is removed or obscured, since the original label is no longer accurate once the resulting final suspension is completed. The contents of the bottle need to be shaken well before taken as directed by the medical professional.

Store the unused kit at room temperature of 15-30°C (59-86°F). once prepared, store the mixed suspension between 2-8°C (36-46°F). The resulting final suspension is stable for up to eight weeks, based upon real-time and accelerated stability studies.

An oral dispenser is provided in the kit and may be used to facilitate delivery of the suspension.

U.S. Patents Pending

Repackaged and Distributed by:

California Pharmaceuticals LLC

768 Calle Plano

Camrillo, CA 93012

California

PHARMACEUTICALS LLC

CS43-A1 rev 3

Ranitidine Hydrochloride Product Label

Do not use if safety seal is broken

Ranitidine Hydrochloride

1, 1-Ethenediamine, N-[2-[[[5-[(dimethylamino)methyl]-2furanyl]-methyl]thio]ehtyl]-N-methyl-2-nitro, monohydrochloride

CAS # 66357-59-3

Net contents: 6.4 g

Repackaged by:

California Pharmaceuticals, LLC

Camarillo, CA 93012

California

PHARMACEUTICALS

CS130-A1 rev 1

Oral Suspension Label

Do not use if safety seal is broken

Pineapple/Orange Oral Suspension Vehicle

Sugar, dye, and paraben free

Ingredients: purified water, glycerin, xylitol, monoammoniumium glycyrrhizinate, pineapple flavor, orange flavor, potassium sorbate, xanthan gum, sodium benzoate, citric acid, sodium citrate

Net contents: 250 mL (8.4 fl oz)

Manufactured for:

California Pharmaceuticals LLC

Camarillo, Ca 3012

California

PHARMACEUTICALS LLC

CS36-A-1 rev 2

Ranitidine Hydrochloride Oral Suspension Pineapple/Orange Oral Suspension Kit Label

NDC 70332-109-01

Rx only

Ranitidine Hydrochloride Oral Suspension and Pineapple/Orange Oral Suspension Kit

(ranitidine hydrochloride 25.0 mg/mL [equivalent to 22.4 mg/mL rantidine],

in a Pineapple/Orange oral suspension kit) Histamine-2 blocker

Description:

This kit contains active and inactive materials to prepare 250mL of a ranitidine hydochloride Pineapple/Orange oral suspension containing 25.0 mg/mL ranitidine hydrochloride [equivalent to 22.4 mg/mL ranitidine]. This kit may only be used for prescriptioncompounding by an appropriate licensed medical professional, in response to a physician's prescription, to create a medication tailored to the specialized needs of an individual patient.

Active Ingredients:

- 6.4 ranitidine hydrochloride USP [equivalent to 5.7 g ranitidine]

Inactive Ingredients:

- 250mL Pineapple/Orange oral suspension vehicle (purified water, glycerin, xylitol, monoammoniumium glycyrrhizinate, pineapple flavor,

orange flavor, potassium sorbate, xanthan gum, sodium benzoate, citric acid, sodium

citrate)

- Press-in bottle adaptor

- Oral dispenser

- Instructions

U. S. Patents Pending

Do not use if safety seal is broken

Store kit at room temperature,

15-30°C (59-86°F).

California

PHARMACEUTICALS LLC

Repackaged and Distributed by:

California Pharmaceuticals, LLC

768 Calle Plano

Camarillo, Ca 93012

CS129-A1 rev 2